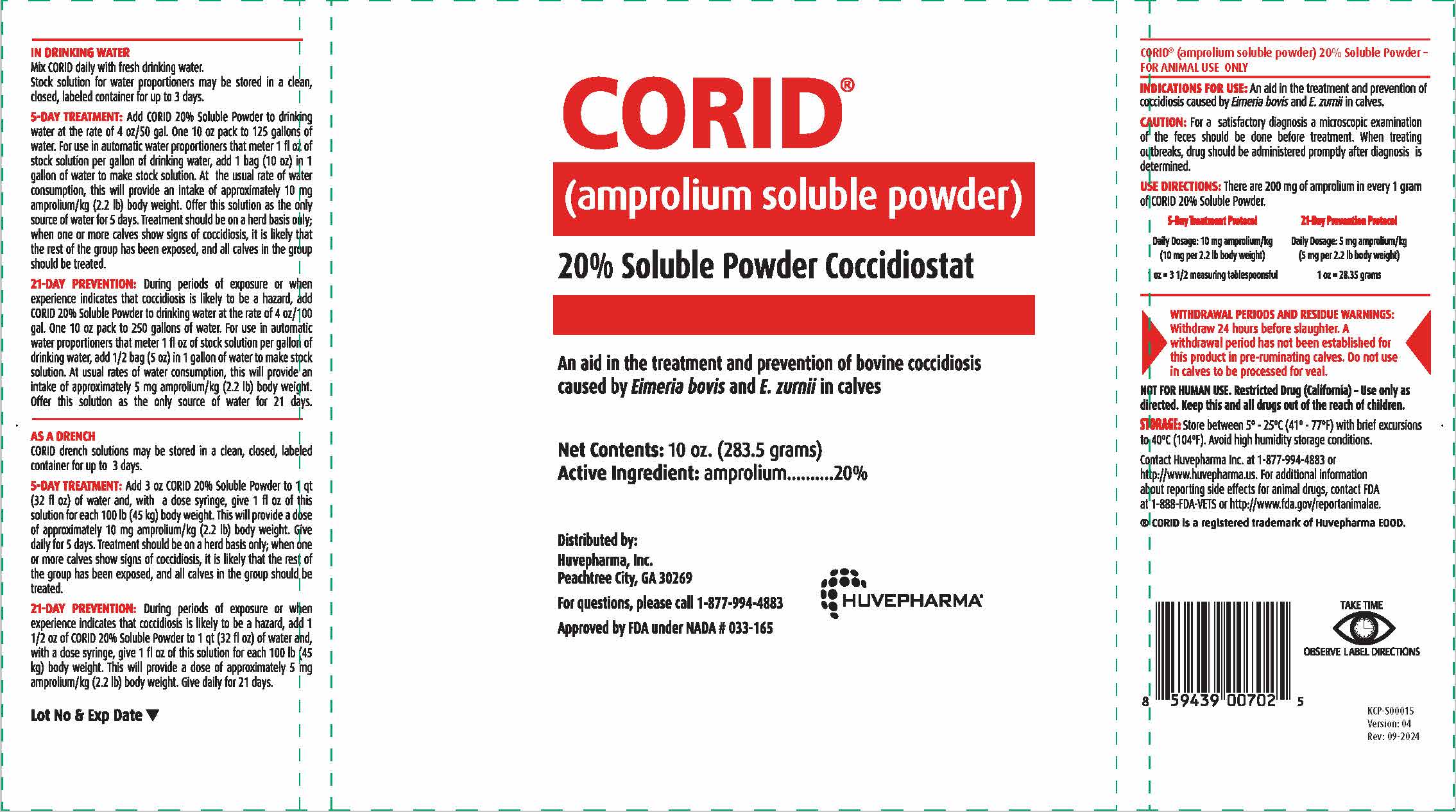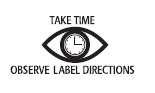 DRUG LABEL: CORID
NDC: 23243-2309 | Form: POWDER, FOR SOLUTION
Manufacturer: Huvepharma, Inc
Category: animal | Type: OTC ANIMAL DRUG LABEL
Date: 20241031

ACTIVE INGREDIENTS: amprolium ion 200 mg/1 g

CORID®
(amprolium soluble powder)
20% Soluble Powder Coccidiostat

An aid in the treatment and prevention of bovine coccidiosis
caused by Eimeria bovis and E. zurnii in calves

ACTIVE INGREDIENT

Net Contents: 10 oz. (283.5 grams)
Active Ingredient: amprolium……….20%

Distributed by:
Huvepharma, Inc.
Peachtree City, GA 30269

For questions, please call 1-877-994-4883
Approved by FDA under NADA # 033-165

DOSAGE AND ADMINISTRATION

IN DRINKING WATER
Mix CORID daily with fresh drinking water.
Stock solution for water proportioners may be stored in a clean,
closed, labeled container for up to 3 days.

5-DAY TREATMENT: Add CORID 20% Soluble Powder to drinking
water at the rate of 4 oz/50 gal. One 10 oz pack to 125 gallons of
water. For use in automatic water proportioners that meter 1 fl oz of
stock solution per gallon of drinking water, add 1 bag (10 oz) in 1
gallon of water to make stock solution. At the usual rate of water
consumption, this will provide an intake of approximately 10 mg
amprolium/kg (2.2 lb) body weight. Offer this solution as the only
source of water for 5 days. Treatment should be on a herd basis only;
when one or more calves show signs of coccidiosis, it is likely that
the rest of the group has been exposed, and all calves in the group
should be treated.

21-DAY PREVENTION: During periods of exposure or when
experience indicates that coccidiosis is likely to be a hazard, add
CORID 20% Soluble Powder to drinking water at the rate of 4 oz/100
gal. One 10 oz pack to 250 gallons of water. For use in automatic
water proportioners that meter 1 fl oz of stock solution per gallon of
drinking water, add 1/2 bag (5 oz) in 1 gallon of water to make stock
solution. At usual rates of water consumption, this will provide an
intake of approximately 5 mg amprolium/kg (2.2 lb) body weight.
Offer this solution as the only source of water for 21 days.

DOSAGE AND ADMINISTRATION

AS A DRENCH
CORID drench solutions may be stored in a clean, closed, labeled
container for up to 3 days.

5-DAY TREATMENT: Add 3 oz CORID 20% Soluble Powder to 1 qt
(32 fl oz) of water and, with a dose syringe, give 1 fl oz of this
solution for each 100 lb (45 kg) body weight. This will provide a dose
of approximately 10 mg amprolium/kg (2.2 lb) body weight. Give
daily for 5 days. Treatment should be on a herd basis only; when one
or more calves show signs of coccidiosis, it is likely that the rest of
the group has been exposed, and all calves in the group should be
treated.

21-DAY PREVENTION: During periods of exposure or when
experience indicates that coccidiosis is likely to be a hazard, add 1
1/2 oz of CORID 20% Soluble Powder to 1 qt (32 fl oz) of water and,
with a dose syringe, give 1 fl oz of this solution for each 100 lb (45
kg) body weight. This will provide a dose of approximately 5 mg
amprolium/kg (2.2 lb) body weight. Give daily for 21 days.

Lot No & Exp Date

VETERINARY INDICATIONS

CORID® (amprolium soluble powder) 20% Soluble Powder -
FOR ANIMAL USE ONLY

INDICATIONS FOR USE: An aid in the treatment and prevention of coccidiosis
caused by Eimeria bovis and E. zurnii in calves.

PRECAUTIONS

CAUTION: For a satisfactory diagnosis a microscopic examination
of the feces should be done before treatment. When treating
outbreaks, drug should be administered promptly after diagnosis is
determined.

USE DIRECTIONS: There are 200 mg of amprolium in every 1 gram
of CORID 20% Soluble Powder.

5-Day Treatment Protocol | 21-Day Prevention Protocol
Daily Dosage: 10 mg amprolium/kg; (10 mg per 2.2 lb body weight) | Daily Dosage: 5 mg amprolium/kg; (5 mg per 2.2 lb body weight)
1 oz = 3 1/2 measuring tablespoonsful | 1 oz = 28.35 grams

WITHDRAWAL PERIODS AND RESIDUE WARNINGS: Withdraw 24 hours
before slaughter. A withdrawal period has not been established for this
product in pre-ruminating calves. Do not use in calves to be processed
for veal.

USER SAFETY WARNINGS

NOT FOR HUMAN USE. Resticted Drug (California)- Use only as
directed. Keep this and all drugs out of the reach of children.

STORAGE AND HANDLING

STORAGE: Store between 5º - 25ºC (41º - 77ºF) with brief excursions
to 40ºC (104ºF). Avoid high humidity storage conditions.

ADVERSE REACTIONS

Contact Huvepharma Inc. at 1-877-994-4883 or
http://www.huvepharma.us. For additional information
about reporting side effects for animal drugs, contact FDA
at 1-888-FDA-VETS or http://www.fda.gov/reportanimalae.

® CORID is a registered trademark of Huvepharma EOOD.